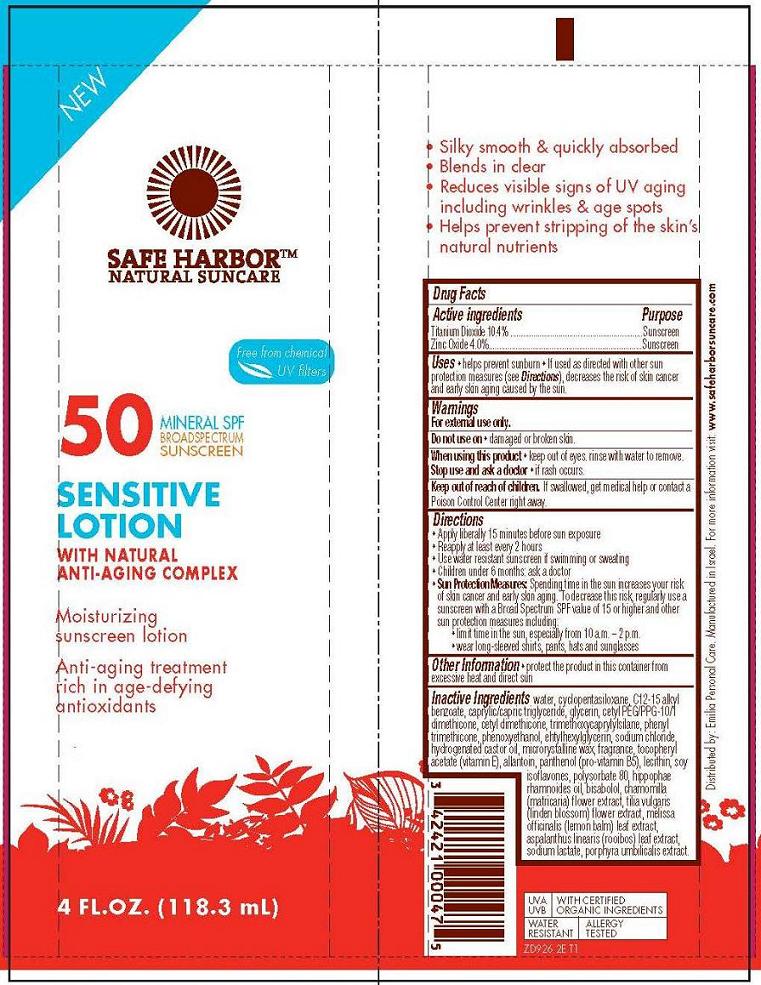 DRUG LABEL: Safe Harbor - Natural - Sensitive SPF50 Broad Spectrum
NDC: 42421-926 | Form: LOTION
Manufacturer: Emilia Personal Care Inc.
Category: otc | Type: HUMAN OTC DRUG LABEL
Date: 20131119

ACTIVE INGREDIENTS: TITANIUM DIOXIDE 10.4 g/100 mL; ZINC OXIDE 4 g/100 mL
INACTIVE INGREDIENTS: WATER; CYCLOMETHICONE 5; ALKYL (C12-15) BENZOATE; TRICAPRYLIN; GLYCERIN; CETYL PEG/PPG-10/1 DIMETHICONE (HLB 2); CETYL DIMETHICONE 150; TRIMETHOXYCAPRYLYLSILANE; PHENYL TRIMETHICONE; PHENOXYETHANOL; ETHYLHEXYLGLYCERIN; SODIUM CHLORIDE; HYDROGENATED CASTOR OIL; MICROCRYSTALLINE WAX; .ALPHA.-TOCOPHEROL ACETATE; ALLANTOIN; PANTHENOL; LECITHIN, SOYBEAN; SOY ISOFLAVONES; POLYSORBATE 80; HIPPOPHAE RHAMNOIDES FRUIT OIL; LEVOMENOL; CHAMOMILE; TILIA X EUROPAEA FLOWER; MELISSA OFFICINALIS LEAF; ASPALATHUS LINEARIS LEAF; SODIUM LACTATE; PORPHYRA UMBILICALIS

Safe Harbor Natural Suncare

Active ingredient

Titanium Dioxide 10.4%
Zinc Oxide 4.0%

Purpose

Sunscreen

Uses

- helps prevent sunburn
- If used as directed with other sun protections measures (see Directions), decreases the risk of skin cancer and early skin aging caused by the sun.

Warnings

For external use only.

Do not use on

- damaged or broken skin

When using this product

- keep out of eyes. rinse with water to remove

Stop use and ask a doctor

- if rash occurs

Keep Out of Reach of Children

If swallowed, get medical help or contact a Poison Control Center right away.

Directions

- Apply liberally 15 minutes before sun exposure
- Reapply at least every 2 hours
- Use water resistant sunscreen if swimming or sweating
- Children under 6 months: ask a doctor
- Sun Protection Measures: Spending time in the sun increases your risk of sun cancer and early skin aging. To decrease this risk, regularly use a sunscreen with a Broad Spectrum SPF value of 15 or higher and other sun protection measures including:
  - limit time in the sun, especially from 10a.m. - 2p.m.
  - wear long-sleeved shirts, pants, hats, and sunglasses

Other information

- protect the product in this container from excessive heat and direct sun

Inactive ingredients

water, cyclopentasiloxane, C12-15 alkyl benzoate, caprylic/capric triglyceride, glycerin, cetyl PEG/PPG-10/1 dimethicone, cetyl dimethicone, trimethoxycaprylylsilane, phenyl trimethicone, phenoxyethanol, ethylhexylglycerin, sodium chloride, hydrogenated castor oil, microcrystaline wax, tocopheryl acetate (vitamin E), allantoin, panthenol (pro-vitamin B5), lecithin, soy isoflavones, polysorbate 80, hippophae rhamnoides oil, bisabolol, camomilla recutita (matricaria) flower extract, tilia vulgaris (linden blossom) flower extract, melissa officinalis (lemon balm) leaf extract, aspalanthus linearis (rooibos) leaf extract, sodium lactate, porphyra umbilicalis extract

Package/Label Principal Display Panel

Safe Harbor™ Natural Suncare

Free from chemical UV filters

50 Mineral SPF Broad Spectrum Sunscreen

Sensitive Lotion
With Natural Anti-Aging Complex

Moisturizing sunscreen lotion

Anti-aging treatment
rich in age-defying antioxidants

4 Fl. Oz (118.3 mL)

Distributed by: Emilia Personal Care.
Manufactured in Israel.
For more information visit: www.safeharborsuncare.com

UVA, UVB
With Certified Organic Ingredients
Water Resistant
Allergy Tested

ZD926 2E T1

Label